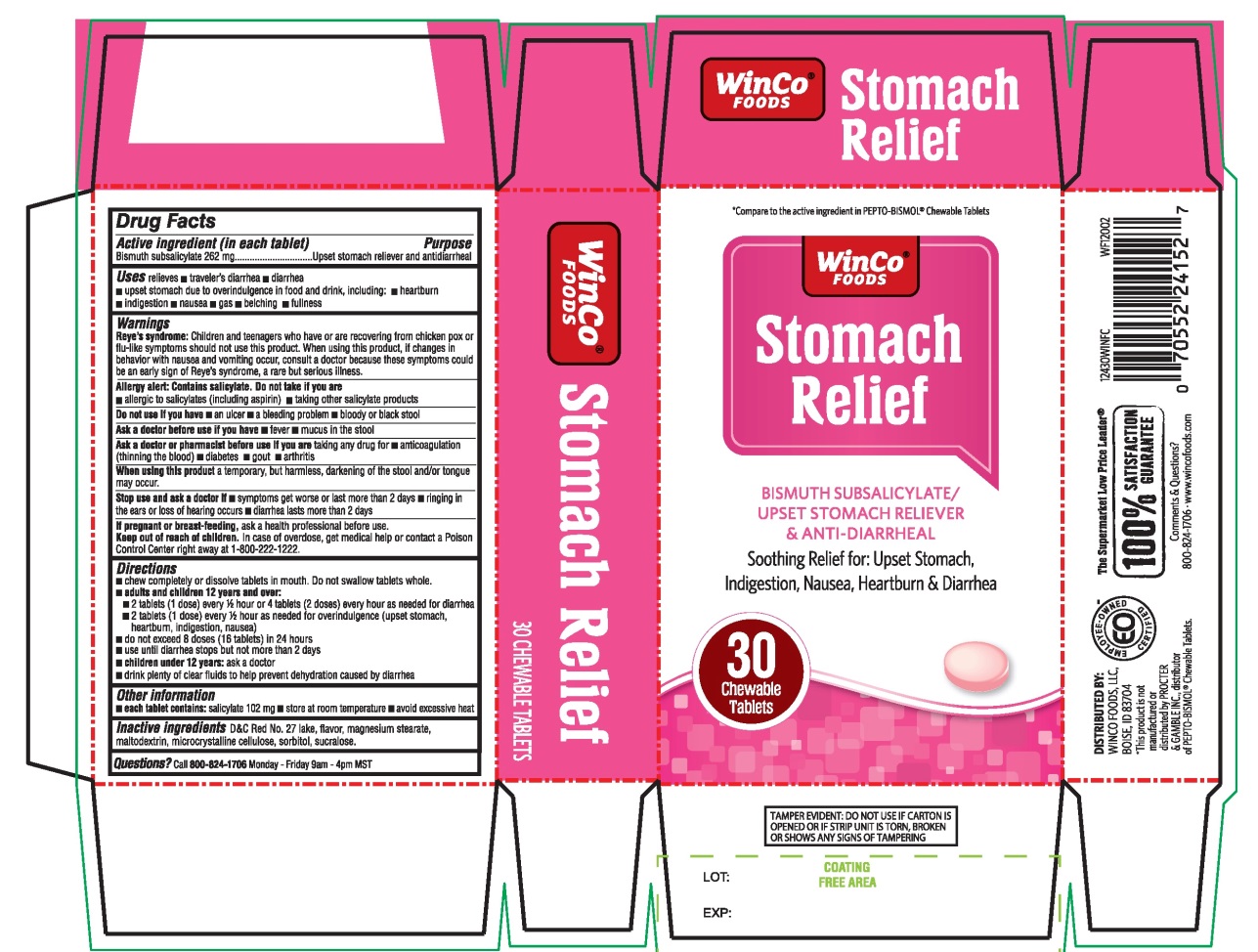 DRUG LABEL: WinCo FOODS Stomach Relief
NDC: 67091-364 | Form: TABLET, CHEWABLE
Manufacturer: WINCO FOODS LLC
Category: otc | Type: HUMAN OTC DRUG LABEL
Date: 20251202

ACTIVE INGREDIENTS: BISMUTH SUBSALICYLATE 262 mg/1 1
INACTIVE INGREDIENTS: D&C RED NO. 27; MAGNESIUM STEARATE; MALTODEXTRIN; MICROCRYSTALLINE CELLULOSE; SORBITOL; SUCRALOSE

Winco FOODS Stomach Relief Bismuth Subsalicylate 30 Chewable Tablets

Active ingredient (in each tablet)

Bismuth subsalicylate 262 mg

Purpose

Upset stomach reliever and antidiarrheal

Uses

relieves:

- travelers’ diarrhea
- diarrhea
- upset stomach due to overindulgence in food and drink, including:
- heartburn
- indigestion
- nausea
- gas
- belching
- fullness

Warnings

Reye's syndrome:Children and teenagers who have or are recovering from chicken pox or flu-like symptoms should not use this product. When using this product, if changes in behavior with nausea and vomiting occur, consult a doctor because these symptoms could be an early sign of Reye's syndrome, a rare but serious illness.

Allergy alert: Contains salicylate. Do not take if you are

- allergic to salicylates (including aspirin)
- taking other salicylate products

Do not use if you have

- an ulcer
- a bleeding problem
- bloody or black stool

Ask a doctor before use if you have

- fever
- mucus in the stool

Ask a doctor or pharmacist before use if you aretaking any drug for

- anticoagulation (thinning of the blood)
- diabetes
- gout
- arthritis

When using this product

a temporary, but harmless, darkening of the stool and/or tongue may occur.

Stop use and ask a doctor if

- symptoms get worse or last more than 2 days
- ringing in the ears or loss of hearing occurs
- diarrhea lasts more than 2 days

If pregnant or breast-feeding,ask a health professional before use .

Keep Out of Reach of Children

In case of overdose, get medical help or contact a Poison Control Center immediately at 1-800-222-1222

Directions

- chew completely or dissolve tablets in mouth. Do not swallow tablets whole.
- adults and children 12 years and over:2 tablets (1 dose) every ½ hour or 4 tablets (2 doses) every hour as needed for diarrhea
- 2 tablets (1 dose) every ½ hour as needed for overindulgence (upset stomach, heartburn, indigestion, nausea)
- do not exceed 8 doses (16 tablets) in 24 hours
- use until diarrhea stops but not more than 2 days
- children under 12 years:ask a doctor
- drink plenty clear fluids to help prevent dehydration caused by diarrhea.

Other information

- each tablet contains: salicylate 102 mg
- store at room temperature.
- avoid excessive heat
- keep this carton for future reference on full labeling

TAMPER EVIDENT: Do not use if printed inner wrap is broken or missing.

Inactive ingredients

D&C Red No. 27 lake, flavor, magnesium stearate, maltodextrin, microcrystalline cellulose, sorbitol, sucralose.

Questions?

Call 800-824-1706 Monday – Friday 9am – 4pm MST

Principal Display

Winco®FOODS

NDC# 67091-364-30

Compare to the active ingredient in PEPTO-BISMOL®Chewable Tablets

Stomach Relief

BISMUTH SUBSALICYLATE/

UPSET STOMACH RELIEVER & ANTI-DIARRHEAL

Soothing Relief for: Upset stomach, Indigestion, Nausea, Heartburn, Diarrhea

The Supermarket Low Price Leader®

100% SATISFACTION GUARANTEE

Comments & Question?

800-824-1706 www.wincofoods.com

30 Chewable Tablets

DISTRIBUTED BY:

WINCO FOODS, LLC,

BOISE, ID 83704

*This product is not manufactured or distributed by PROCTER & GAMBLE INC., distributor of PEPTO-BISMOL® Chewable Tablets

If any reason you are not satisfied with this product, please return it to the store where purchased for a full refund.